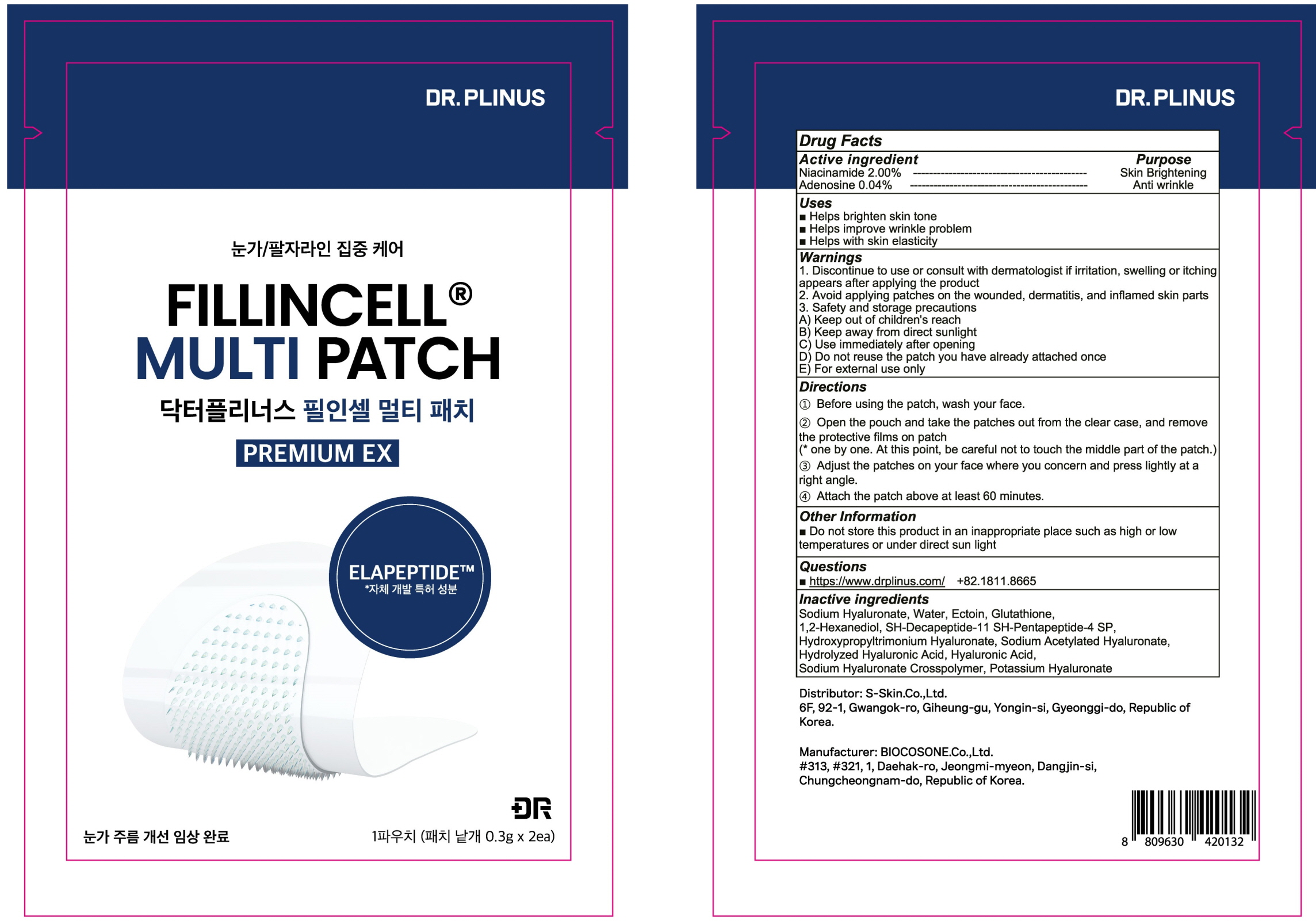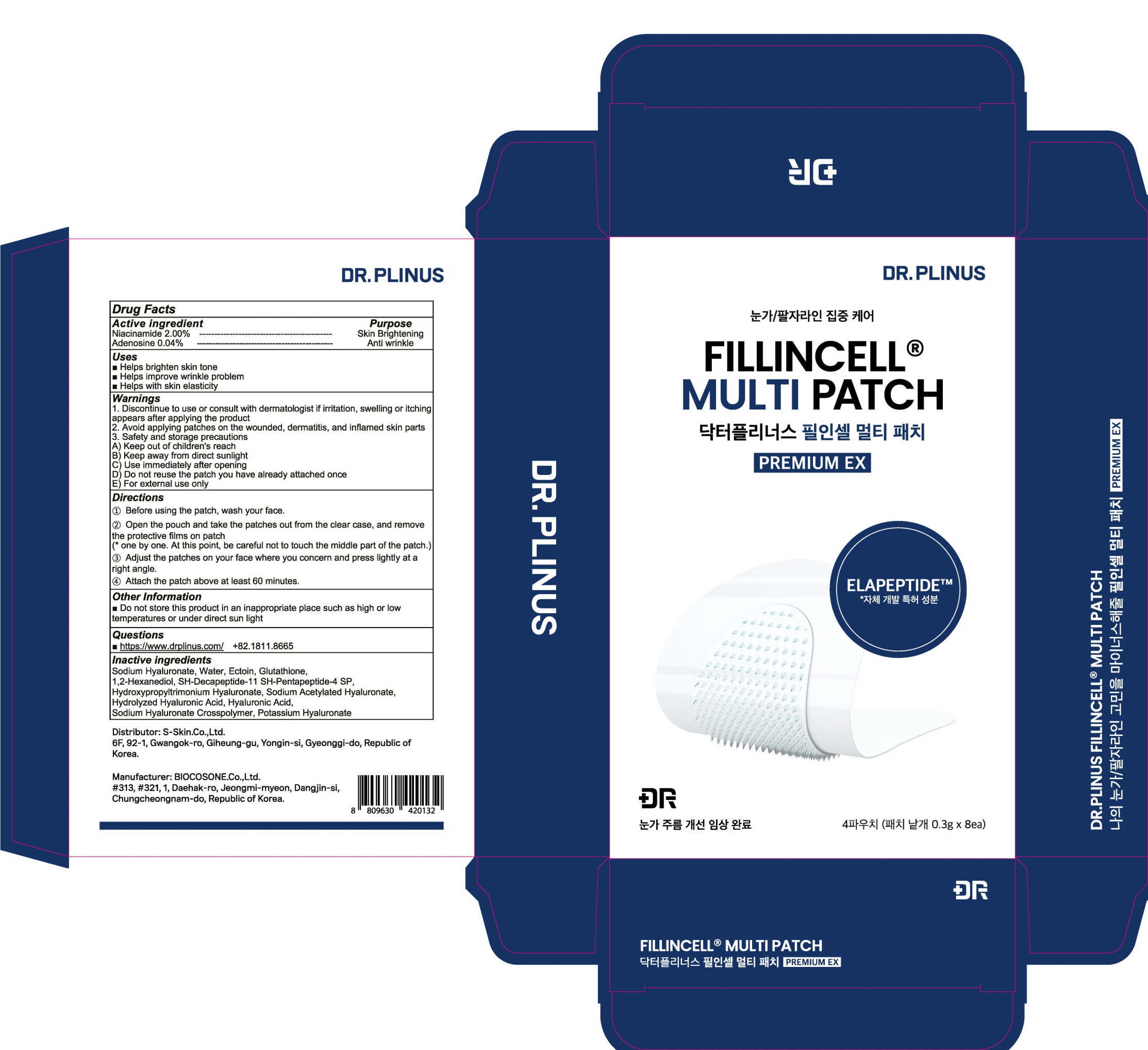 DRUG LABEL: DR.PLINUS FILLINCELL MULTI EX
NDC: 72630-040 | Form: PATCH
Manufacturer: S Skin Co., Ltd.
Category: otc | Type: HUMAN OTC DRUG LABEL
Date: 20221121

ACTIVE INGREDIENTS: Niacinamide 0.006 g/0.3 g; Adenosine 0.00012 g/0.3 g
INACTIVE INGREDIENTS: HYALURONATE SODIUM; Water

ACTIVE INGREDIENTS

Niacinamide 2.00%
Adenosine 0.04%

INACTIVE INGREDIENTS

Sodium Hyaluronate, Water, Ectoin, Glutathione, 1,2-Hexanediol, SH-Decapeptide-11 SH-Pentapeptide-4 SP, Hydroxypropyltrimonium Hyaluronate, Sodium Acetylated Hyaluronate, Hydrolyzed Hyaluronic Acid, Hyaluronic Acid, Sodium Hyaluronate Crosspolymer, Potassium Hyaluronate

PURPOSE

Skin Brightening
Anti wrinkle

WARNINGS

1. Discontinue to use or consult with dermatologist if irritation, swelling or itching appears after applying the product
2. Avoid applying patches on the wounded, dermatitis, and inflamed skin parts
3. Safety and storage precautions
A) Keep out of children's reach
B) Keep away from direct sunlight
C) Use immediately after opening
D) Do not reuse the patch you have already attached once
E) For external use only

KEEP OUT OF REACH OF CHILDREN

Keep out of children's reach

Uses

■ Helps brighten skin tone
■ Helps improve wrinkle problem
■ Helps with skin elasticity

Directions

① Before using the patch, wash your face.
② Open the pouch and take the patches out from the clear case, and remove the protective films on patch
(* one by one. At this point, be careful not to touch the middle part of the patch.)
③ Adjust the patches on your face where you concern and press lightly at a right angle.
④ Attach the patch above at least 60 minutes.

Other Information

■ Do not store this product in an inappropriate place such as high or low temperatures or under direct sun light

QUESTIONS

■ https://www.drplinus.com/ +82.1811.8665